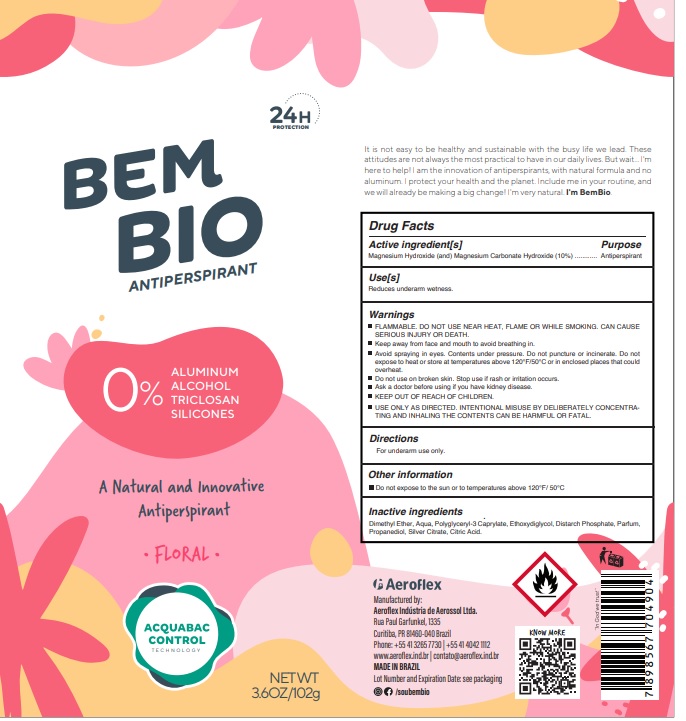 DRUG LABEL: Bem Bio Antiperspirant floral
NDC: 80661-004 | Form: AEROSOL, SPRAY
Manufacturer: Aeroflex Industria de Aerosol Ltda
Category: otc | Type: HUMAN OTC DRUG LABEL
Date: 20251031

ACTIVE INGREDIENTS: MAGNESIUM HYDROXIDE 10 g/100 g; MAGNESIUM CARBONATE HYDROXIDE 10 g/100 g
INACTIVE INGREDIENTS: DIMETHYL ETHER; WATER; POLYGLYCERYL-3 CAPRATE; DIETHYLENE GLYCOL MONOETHYL ETHER; DISTARCH PHOSPHATE, CORN; PROPANEDIOL; SILVER CITRATE; CITRIC ACID MONOHYDRATE

Active Ingredients

Magnesium Hydroxide (and) Magnesium Carbonate Hydroxide
(10%)

Purpose

Antiperspirant

Uses

Reduces underarm wetness.

Warnings

FLAMMABLE. DO NOT USE NEAR HEAT, FLAME OR WHILE SMOKING. CAN
CAUSE SERIOUS INJURY OR DEATH.
Keep away from face and mouth to avoid breathing in.
Avoid spraying in eyes. Contents under pressure. Do not puncture or incinerate. Do not
expose to heat or store at temperatures above 120°F/50°C or in enclosed places that could
overheat.
Do not use on broken skin. Stop use if rash or irritation occurs.
Ask a doctor before using if you have kidney disease.
KEEP OUT OF REACH OF CHILDREN.
USE ONLY AS DIRECTED. INTENTIONAL MISUSE BY DELIBERATELY
CONCENTRATING AND INHALING THE CONTENTS CAN BE HARMFUL OR
FATAL.

Directions

For underarm use only.

Other Information

Do not expose to the sun or to temperatures above 120°F/ 50°C

Inactive Ingredients

Dimethyl Ether, Aqua, Polyglyceryl-3 Caprylate, Ethoxydiglycol, Distarch Phosphate, Parfum, Propanediol, Silver Citrate, Citric Acid.